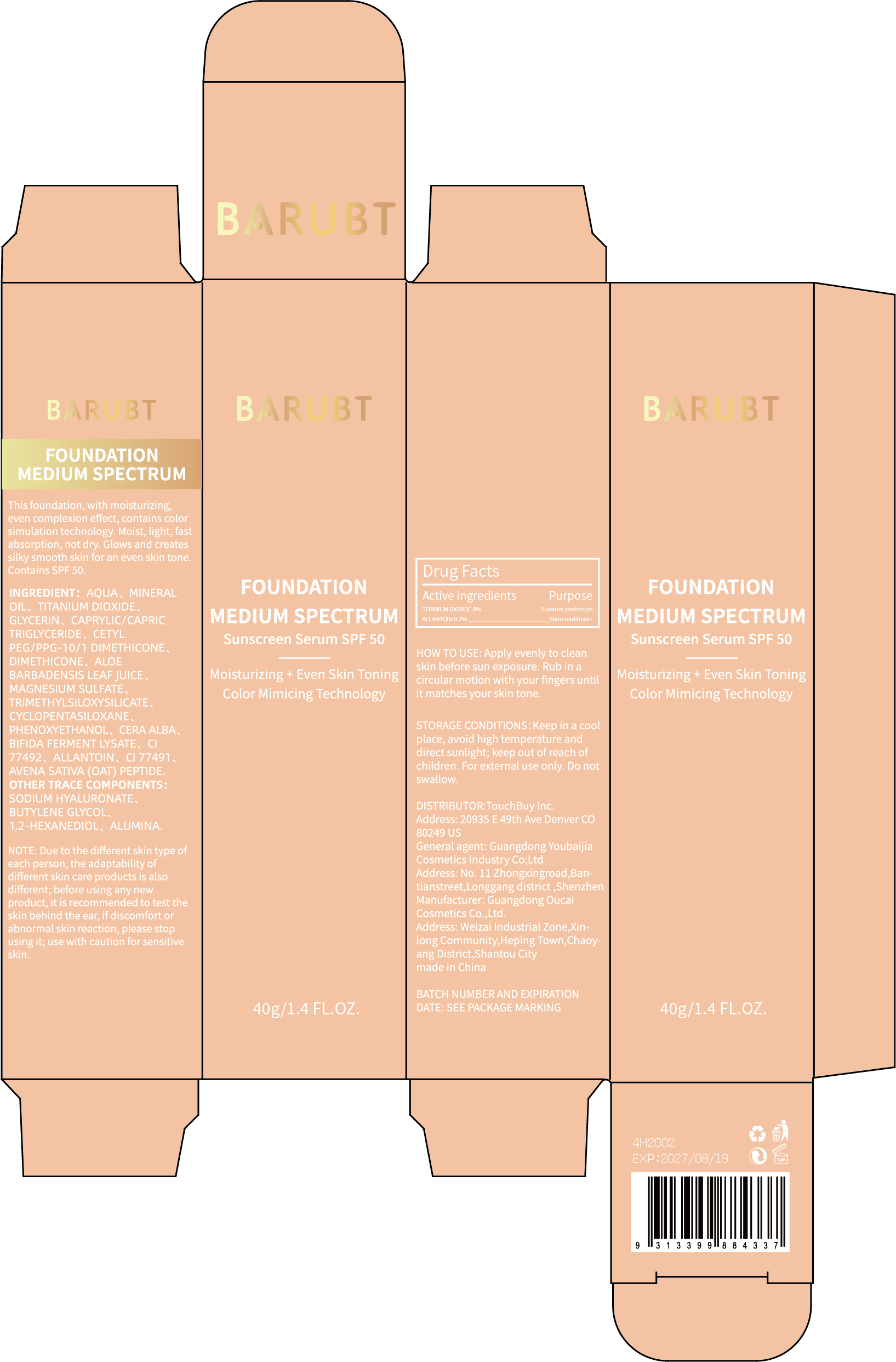 DRUG LABEL: BARUBT FOUNDATION MEDIUM SPECTRUM
NDC: 84712-025 | Form: CREAM
Manufacturer: Guangdong Youbaijia Cosmetic Industry Co., Ltd
Category: otc | Type: HUMAN OTC DRUG LABEL
Date: 20250107

ACTIVE INGREDIENTS: TITANIUM DIOXIDE 3.2 g/40 g; ALLANTOIN 0.08 g/40 g
INACTIVE INGREDIENTS: MINERAL OIL 4.4 g/40 g; GLYCERIN 2.4 g/40 g

ACTIVE INGREDIENT

TITANIUM DIOXIDE 8%
ALLANTOIN 0.2%

INACTIVE INGREDIENT

AQUA
MINERAL OIL
GLYCERIN
CAPRYLIC/CAPRIC TRIGLYCERIDE
CETYL PEG/PPG-10/1 DIMETHICONE
DIMETHICONE
ALOE BARBADENSIS LEAF JUICE
MAGNESIUM SULFATE
TRIMETHYLSILOXYSILICATE
CYCLOPENTASILOXANE
PHENOXYETHANOL
CERA ALBA
BIFIDA FERMENT LYSATE
CI 77492
CI 77491
AVENA SATIVA (OAT) PEPTIDE
ALUMINA
BUTYLENE GLYCOL
1,2-HEXANEDIOL
SODIUM HYALURONATE

Do not use on damaged skin.

Keep away from children. Do not swallow.

PURPOSE

Sunscreen

QUESTIONS

Contact name: Jessie Peng
Company phone number: +1 818 579 7288
Company e-mail: jessie@registeragentllc.com

STOP USE

lf skin becomes red or irritated, discontinue use immediately and wash with water.

WHEN USING

keep out of eyes. Rinse with water to remove.

STORAGE AND HANDLING

Keep away from light and in a dry place.

WARNINGS

For external use only.

INDICATIONS AND USAGE

This foundation, with moisturizing,even complexion effect, contains color simulation technology. Moist, light, fast absorption,not dry. Glows and creates silky smooth skin for an even skin tone. Contains SPF 50

DOSAGE AND ADMINISTRATION

HOW TO USE: Apply evenly to clean skin before sun exposure. Rub in a circular motion with your fingers until it matches your skin tone.